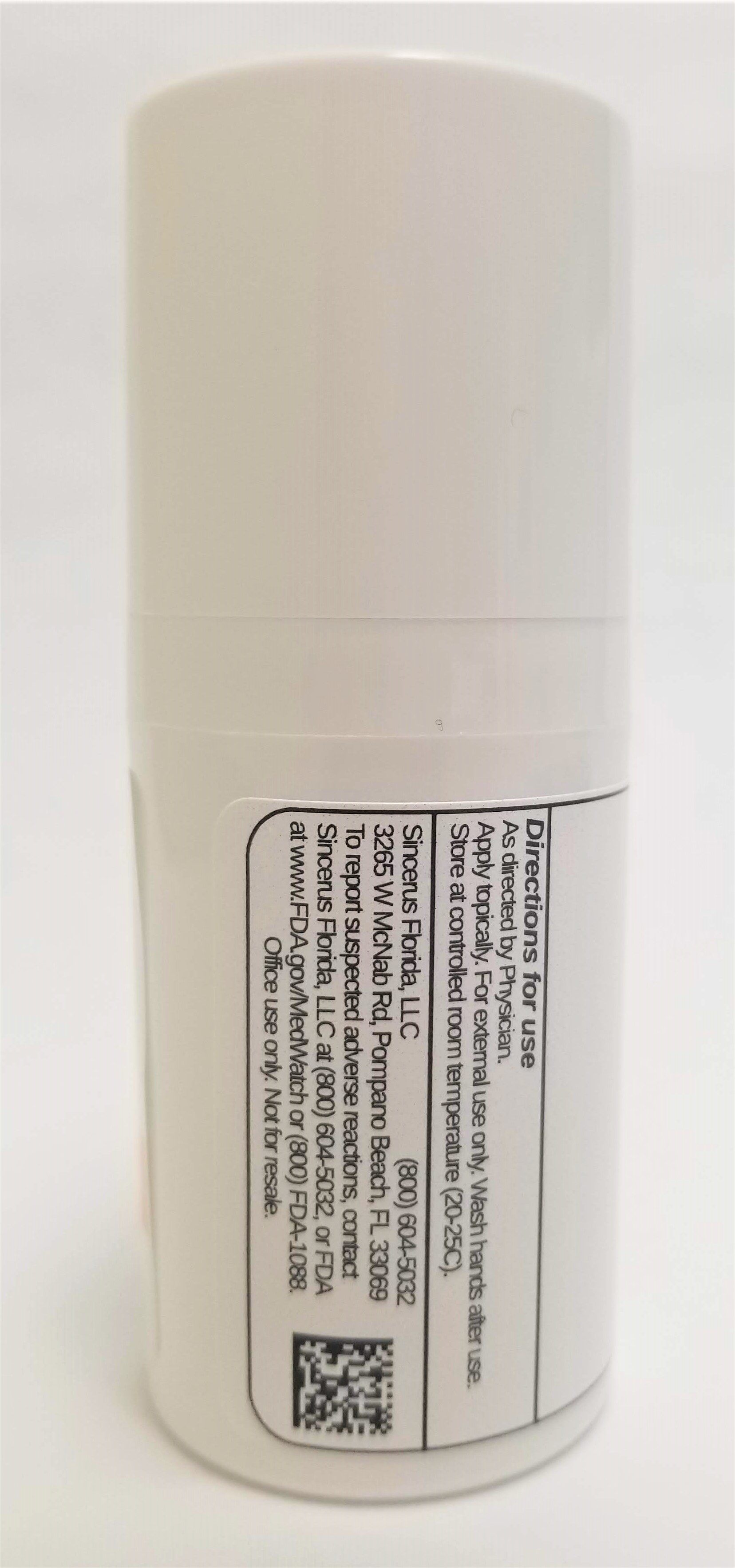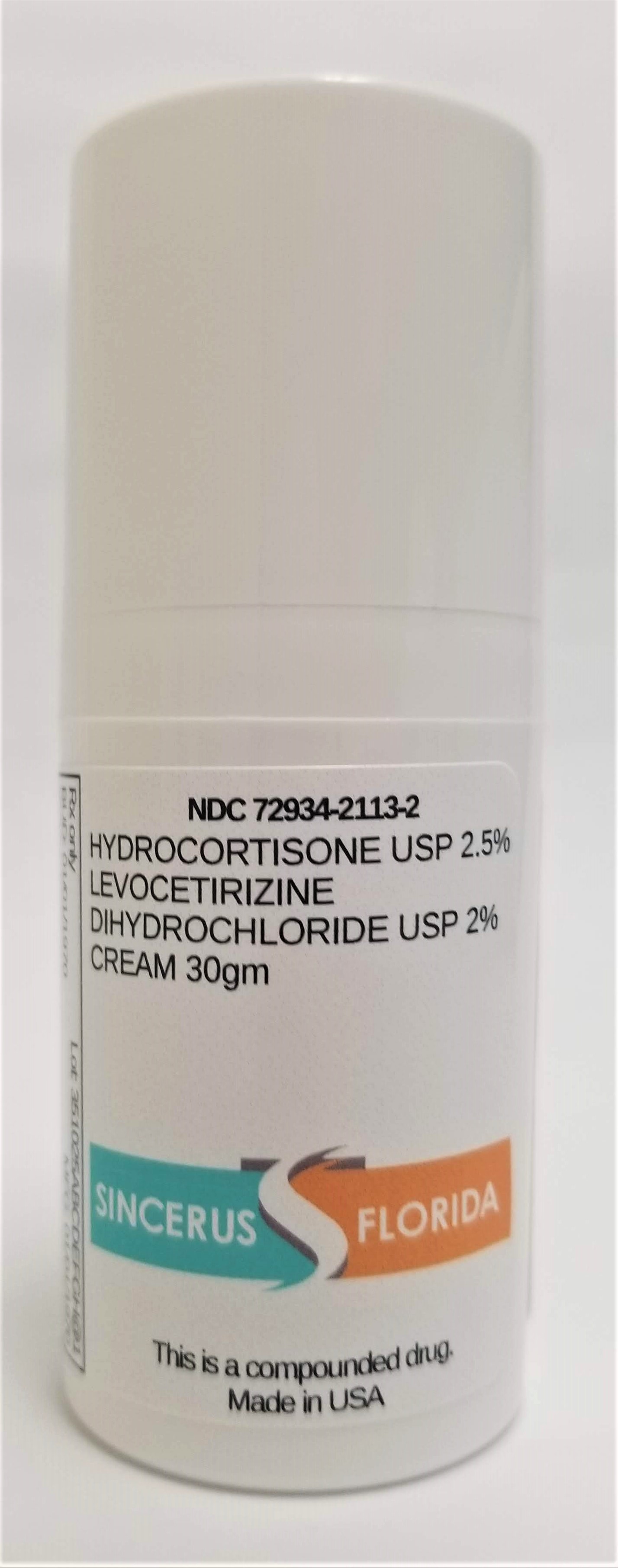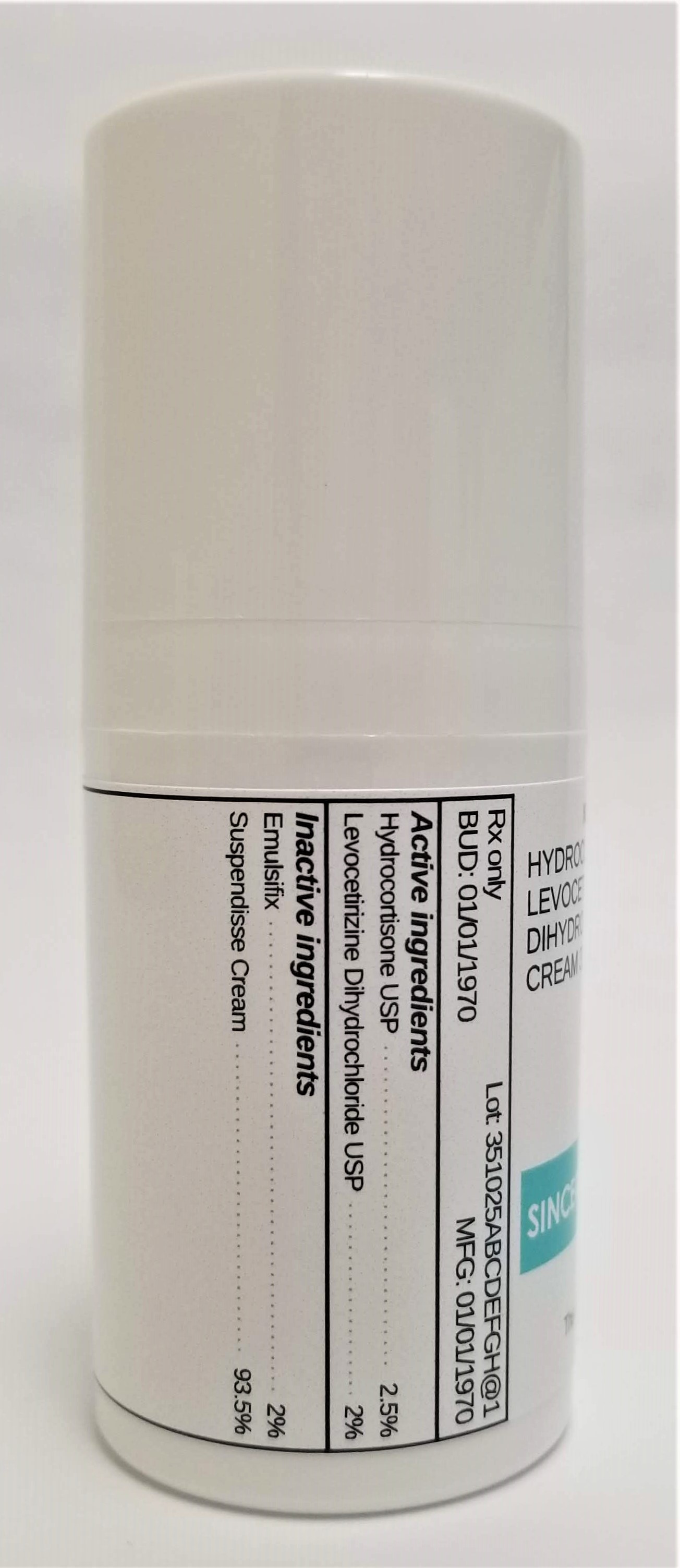 DRUG LABEL: HYDROCORTISONE 2.5% / LEVOCETIRIZINE DIHYDROCHLORIDE 2%
NDC: 72934-2113 | Form: CREAM
Manufacturer: Sincerus Florida, LLC
Category: prescription | Type: HUMAN PRESCRIPTION DRUG LABEL
Date: 20190514

ACTIVE INGREDIENTS: HYDROCORTISONE 2.5 g/100 g; LEVOCETIRIZINE DIHYDROCHLORIDE 2 g/100 g

HYDROCORTISONE 2.5% / LEVOCETIRIZINE DIHYDROCHLORIDE 2%